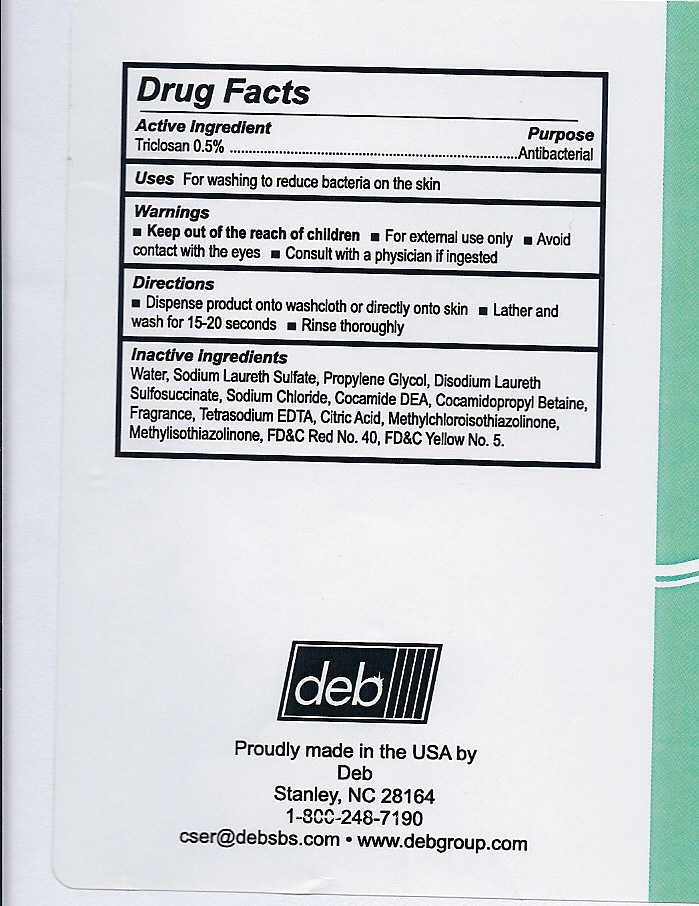 DRUG LABEL: Panache 
NDC: 11084-115 | Form: LIQUID
Manufacturer: Deb USA, Inc.
Category: otc | Type: HUMAN OTC DRUG LABEL
Date: 20110223

ACTIVE INGREDIENTS: Triclosan .55 mL/100 mL
INACTIVE INGREDIENTS: Water; Sodium Laureth Sulfate; Propylene Glycol; Disodium Laureth Sulfosuccinate; Sodium Chloride; COCO DIETHANOLAMIDE    ; Cocamidopropyl Betaine; Edetate Sodium; Anhydrous Citric Acid; FD&C Red No. 40; FD&C Yellow No. 5; Methylchloroisothiazolinone; Methylisothiazolinone

Drug Facts

Active ingredient

Triclosan 0.5%

PURPOSE

Antibacterial

Uses

For washing to decrease bacteria on the skin

Warnings

For external use only

Avoid contact with the eyes

Keep out of reach of children

Consult with a physician if ingested

Directions

Dispense product onto washcloth or directly onto skin

Lather and wash for 15-20 seconds

Rinse thoroughly

INACTIVE INGREDIENT

Water, Sodium Laureth Sulfate, Propylene Glycol, Disodium Laureth Sulfosuccinate, Sodium Chloride, Cocamide DEA, Cocamidopropyl Betaine, Fragrance, Tetrasodium EDTA, Citric Acid, Methylchloroisothiazolinone, Methylisothiazolinone, FDC Red No. 40, FDC Yellow No. 5.